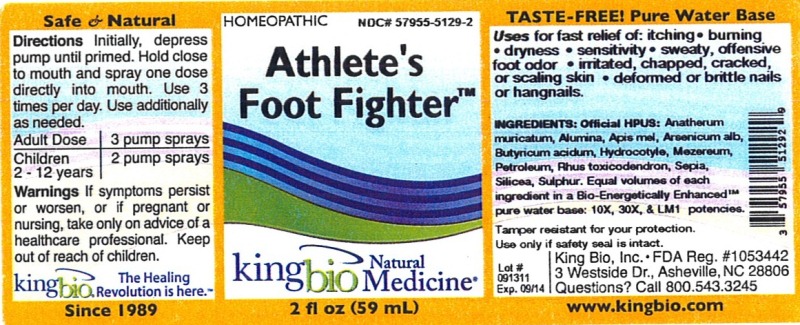 DRUG LABEL: Athletes Foot Fighter
NDC: 57955-5129 | Form: LIQUID
Manufacturer: King Bio Inc.
Category: homeopathic | Type: HUMAN OTC DRUG LABEL
Date: 20120620

ACTIVE INGREDIENTS: VETIVERIA ZIZANIOIDES ROOT 10 [hp_X]/59 mL; ALUMINUM OXIDE 10 [hp_X]/59 mL; APIS MELLIFERA 10 [hp_X]/59 mL; ARSENIC TRIOXIDE 10 [hp_X]/59 mL; BUTYRIC ACID 10 [hp_X]/59 mL; CENTELLA ASIATICA 10 [hp_X]/59 mL; DAPHNE MEZEREUM BARK 10 [hp_X]/59 mL; KEROSENE 10 [hp_X]/59 mL; TOXICODENDRON PUBESCENS LEAF 10 [hp_X]/59 mL; SEPIA OFFICINALIS JUICE 10 [hp_X]/59 mL; SILICON DIOXIDE 10 [hp_X]/59 mL; SULFUR 10 [hp_X]/59 mL
INACTIVE INGREDIENTS: WATER

Athlete's Foot Fighter

Active Ingredients

Official HPUS: Anatherum muricatum, Alumina, Apis mellifica, Arsenicum album, Butyricum acidum, Hydrocotyle asiatica, Mezereum, Petroleum, Rhus toxicodendron, Sepia, Silicea and Sulphur.

Reference image athlete.jpg

Inactive Ingredient

Equal volumes of each ingredient in a Bio-Energetically Enhanced pure water base: 10X, 30X and LM1 potencies

Reference image athlete.jpg

Purpose

Uses for fast relief of:

- itching
- burning
- dryness
- sensitivity
- sweaty, offensive foot odor
- irritated, chapped, cracked or scaling skin
- deformed or brittle nails or hangnails

Reference image athlete.jpg

Dosage and Administration

Directions Initially, depress pump until primed. Hold close to mouth and spray one dose directly into mouth. Use 3 times per day. Use additionally as needed.

Adult Dose 3 pump sprays

Children 2-12 years 2 pump sprays

Reference image athlete.jpg

Warnings

If symptoms persist or worsen, or if pregnant or nursing, take only on advice of a healthcare professional. Keep out of reach of children.

Other: Tamper resistant for your protection. Use only if safety seal is intact.

Reference image athlete.jpg

Keep out of reach of children.

Reference image athlete.jpg

Indications and Usage

Uses for fast relief of: itching, burning, dryness, sensitivity, sweaty, offensive foot odor, irritated, chapped, cracked, or scaling skin, deformed or brittle nails or hangnails.

Reference image athlete.jpg

PACKAGE LABEL

King Bio Inc.

3 Westside Drive

Asheville, NC 28806

Questions? Call 800.543.3245

www.kingbio.com